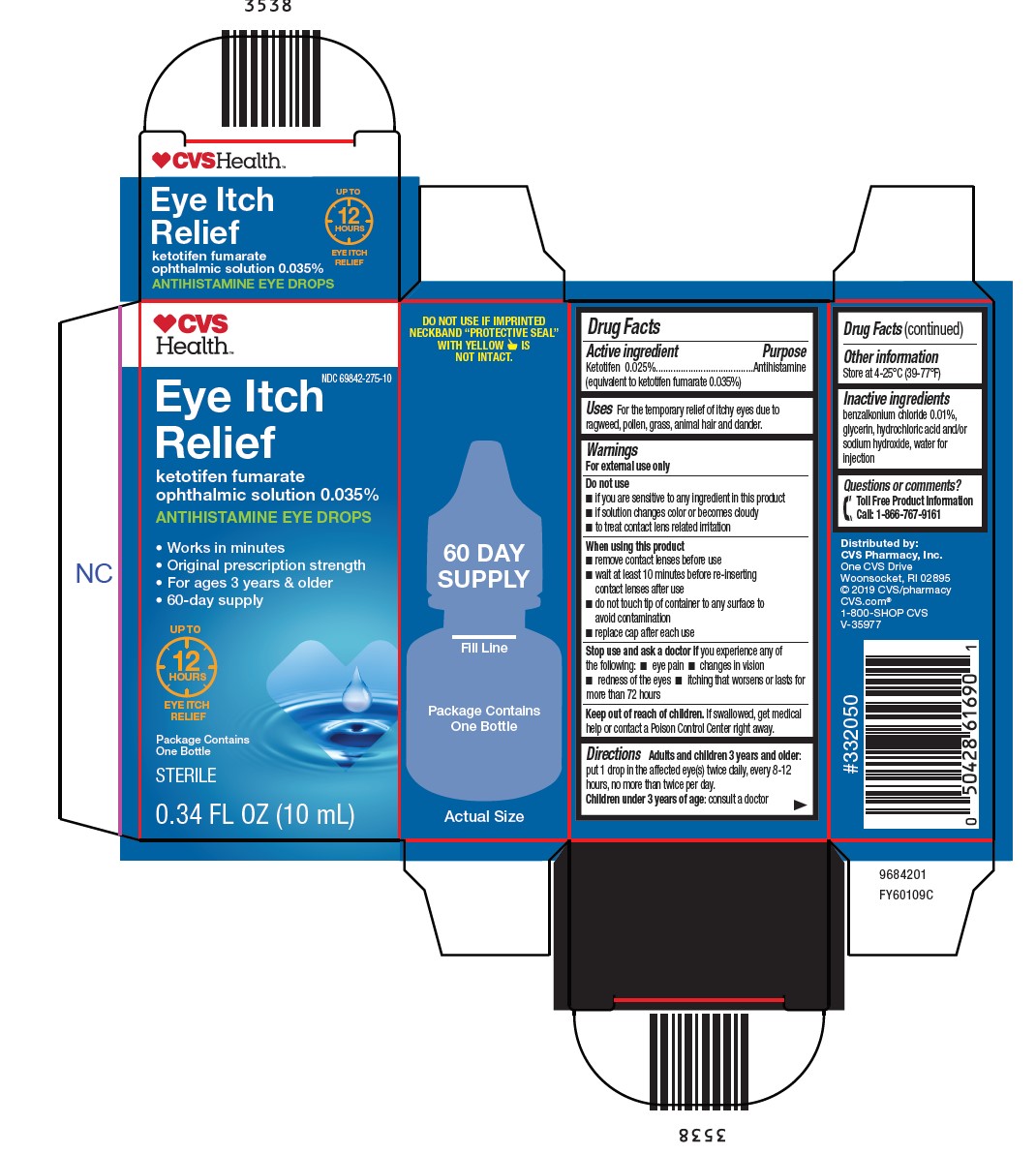 DRUG LABEL: Eye Itch Relief
NDC: 69842-275 | Form: SOLUTION/ DROPS
Manufacturer: CVS Pharmacy
Category: otc | Type: HUMAN OTC DRUG LABEL
Date: 20260115

ACTIVE INGREDIENTS: KETOTIFEN FUMARATE 0.25 mg/1 mL
INACTIVE INGREDIENTS: BENZALKONIUM CHLORIDE; GLYCERIN; HYDROCHLORIC ACID; SODIUM HYDROXIDE; WATER

Drug Facts

Active ingredient

Ketotifen 0.025%
(equivalent to ketotifen fumarate 0.035%)

Purpose

Antihistamine

Uses

For the temporary relief of itchy eyes due to ragweed, pollen, grass, animal hair and dander.

Warnings

For external use only

Do not use

- if you are sensitive to any ingredient in this product
- if solution changes color or becomes cloudy
- to treat contact lens related irritation

When using this product

- remove contact lenses before use
- wait at least 10 minutes before re-inserting contact lenses after use
- do not touch tip of container to any surface to avoid contamination
- replace cap after each use

Stop use and ask a doctor ifyou experience any of the following:

- eye pain
- changes in vision
- redness of the eyes
- itching that worsens or lasts for more than 72 hours

Keep out of reach of children.

If swallowed, get medical help or contact a Poison Control Center right away.

Directions

Adults and children 3 years and older:
put 1 drop in the affected eye(s) twice daily, every 8-12 hours, no more than twice per day.
Children under 3 years of age:consult a doctor

Other information

Store at 4-25°C (39-77°F)

Inactive ingredients

benzalkonium chloride 0.01%, glycerin, hydrochloric acid and/or sodium hydroxide, water for injection

Questions or comments?

[phone icon] Toll Free Product Information
Call: 1-866-767-9161

Package/Label Principal Display Panel

[heart icon] CVS
Health

NDC 69842-275-10

Eye Itch
Relief

ketotifen fumarate
ophthalmic solution 0.035%

ANTIHISTAMINE EYE DROPS

- Works in minutes
- Original prescription strength
- For ages 3 years & older
- 60-day supply

UP TO
12
HOURS
EYE ITCH
RELIEF

Package Contains
One Bottle

STERILE

0.034 FL OZ (10 mL)